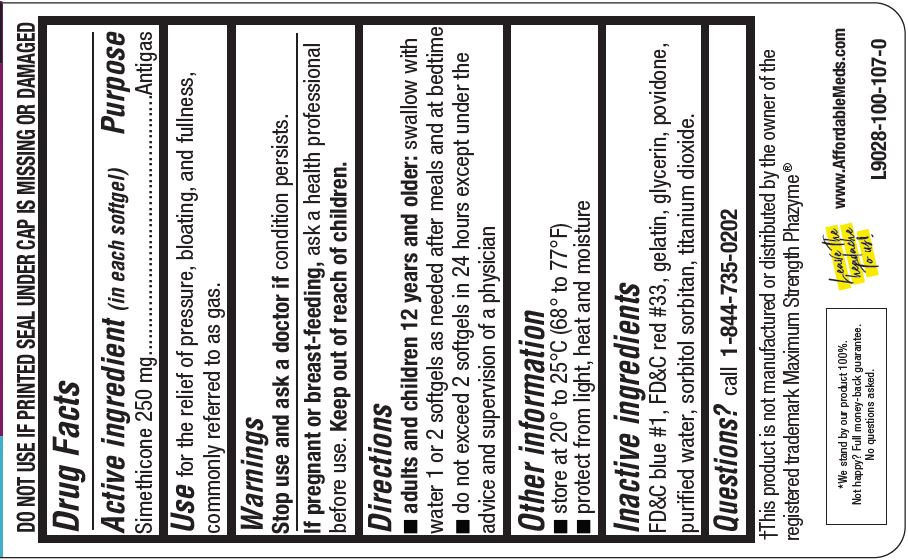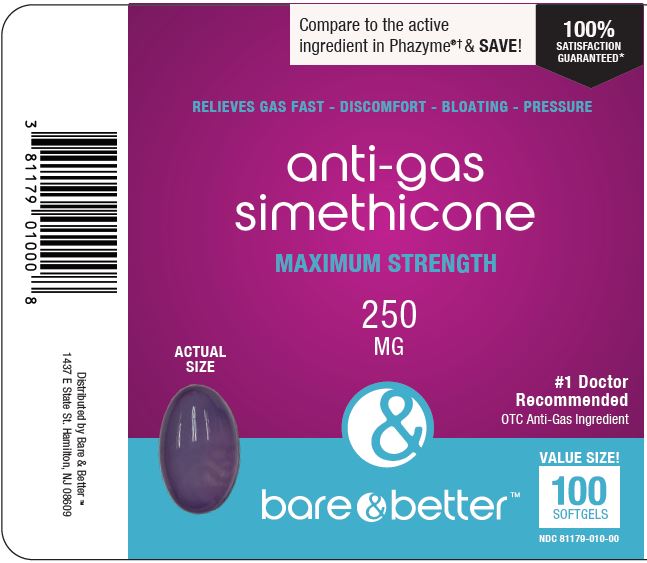 DRUG LABEL: ANTIGAS
NDC: 81179-010 | Form: CAPSULE, LIQUID FILLED
Manufacturer: YET HEALTH GROUP LLC
Category: otc | Type: HUMAN OTC DRUG LABEL
Date: 20240103

ACTIVE INGREDIENTS: DIMETHICONE 250 mg/1 1
INACTIVE INGREDIENTS: FD&C BLUE NO. 1; D&C RED NO. 33; GELATIN; GLYCERIN; POVIDONE; WATER; SORBITOL; SORBITAN; TITANIUM DIOXIDE

YET - BARE & BETTER ANTI-GAS SIMETHICONE - SIMETHICONE 250 MG

Active ingredient (in each softgel)

Simethicone 250 mg

Purpose

Antigas

Uses

for the relief of pressure, bloating, and fullness, commonly referred to as gas.

Warnings

Stop use and ask a doctor if condition persists.
If pregnant or breast-feeding, ask a health professional before use.

Keep out of reach of children.

Directions

- adults and children 12 years and older: swallow with wa ter 1 or 2 softgels as needed after meals and at bedtime
- do not exceed 2 softgels in 24 hours except under the ad vi ce and supervision of a physici an

Other information

■ store at 20° to 25°C (68° to 77°F)
■ protect from light, heat and moisture

Inactive ingredients

D&C blue #1, D&C Red # 33, gelatin, glycerin, povidone, puriﬁed water, sorbitol, sorbitan, titanium dioxide.

Questions?

call 1-844-735-0202